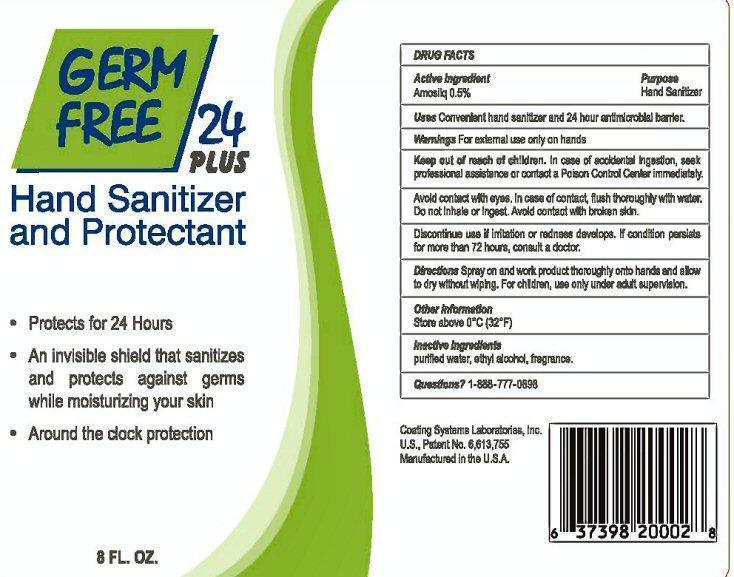 DRUG LABEL: GERM FREE 24 PLUS
NDC: 63377-024 | Form: LIQUID
Manufacturer: Coating Systems Laboratories, Inc.
Category: otc | Type: HUMAN OTC DRUG LABEL
Date: 20130430

ACTIVE INGREDIENTS: BENZALKONIUM CHLORIDE 10 mg/100 mL
INACTIVE INGREDIENTS: WATER; ALCOHOL; DIMETHYLOCTADECYL(3-(TRIMETHOXYSILYL)PROPYL)AMMONIUM CHLORIDE

Active Ingredient

DRUG FACTS
Active Ingredient
AMOSIL-Q 0.5% - Benzalkonium Chloride 0.10%

Purpose

Hand Sanitizer

Keep out of reach of children

In case of accidental ingestion, seek professional assistance or contact a Poison Control Center immediately.

Uses

Convenient hand sanitize and 24 hour antimicrobial barrier.

Warnings

For external use only on hands.

Avoid contact with eyes. In case of contact, flush thoroughly with water.

Do not inhale or ingest. Avoid contact with broken skin.

Discontinue use if irritation or redness develops. If condition persists for more than 72 hours, consult a doctor.

Directions

Spray on and work product thoroughly onto hands and allow to dry without wiping. For children, use only under adult supervision.

Other Information

Store above 0° C (32° F)

Questions?

1-888-777-0898

Inactive ingredients

purified water, ethyl alcohol, fragrance, (3-(Trimethoxysil)Propyl)OctadecyDimethylAmmonium Chloride 0.4%

Product Label

GERM FREE 24 PLUS

Hand Sanitizer and Protectant
Protects for 24 Hours

An invisible shield that sanitizes and protects against germs while moisturizing your skin

Around the clock protection

8 FL. OZ

Coating Systems Laboratories, Inc.

U.S.Patent No.6,613,755

Manufactured in the USA